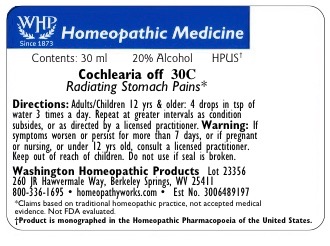 DRUG LABEL: Cochlearia officinalis
NDC: 71919-215 | Form: LIQUID
Manufacturer: Washington Homeopathic Products
Category: homeopathic | Type: HUMAN OTC DRUG LABEL
Date: 20181230

ACTIVE INGREDIENTS: COCHLEARIA OFFICINALIS FLOWERING TOP 30 [hp_C]/1 mL
INACTIVE INGREDIENTS: ALCOHOL; WATER

DRUG FACTS

ACTIVE INGREDIENTS

COCHLEARIA OFF

USES

To relieve the symptoms of radiating stomach pains.

KEEP OUT OF REACH OF CHILDREN

Keep this and all medicines out of reach of children.

INDICATIONS

COCHLEARIA OFF Radiating stomach pains

STOP USE AND ASK DOCTOR

If symptoms persist/worsen or if pregnant/nursing, consult your practitioner.

DIRECTIONS

Adults: 4 drops into a tsp. of water 3 times a day. Children: 1/2 dose. Repeat at greater intervals as condition subsides. Or as directed bya lic. practitioner.

INACTIVE INGREDIENTS

Sucrose/Lactose

PRINCIPAL DISPLAY PANEL

The OTC potency range of COCHLEARIA OFF is 2x–30x, 1c–30c, 200c, 1m, 10m, 50m, and CM.
Availability is subject to change.

All WHP single remedies are made to order; thus, the labels are printed on the same label stock, as the orders are filled.

‘Bottle Size,’ ‘Potency,’ and ‘Alcohol Percentage’ vary on the label depending on customer choice.

Standard bottle sizes for dilution-form remedies are 15ml, 30ml, 50ml, and 100ml.